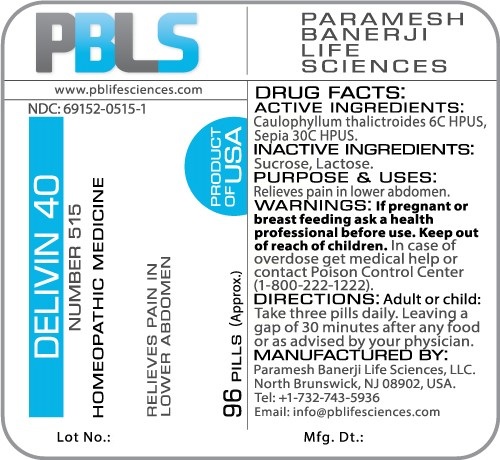 DRUG LABEL: Delivin 40 Number 515
NDC: 69152-0515 | Form: PELLET
Manufacturer: Paramesh Banerji Life Sciences LLC
Category: homeopathic | Type: HUMAN OTC DRUG LABEL
Date: 20160518

ACTIVE INGREDIENTS: CAULOPHYLLUM THALICTROIDES ROOT 6 [hp_C]/1 1; SEPIA OFFICINALIS JUICE 30 [hp_C]/1 1
INACTIVE INGREDIENTS: SUCROSE; LACTOSE

DRUG FACTS: Active Ingredients

Caulophyllum thalictroides 6C HPUS, Sepia 30C HPUS

Inactive Ingredients

Sucrose, Lactose

Purpose

Relieves pain in lower abdomen

Uses

Relieves pain in lower abdomen

Warnings

If pregnant or breast feeding ask a health professional before use.

Keep out of reach of children. In case of overdose, get medical help or contact a Poison Control Center (1-800-222-1222) right away.

Direction

Adult or child: Take three pills daily. Leaving a gap of 30 minutes after any food or as advised by your physician.

Manufactured by

Paramesh Banerji Life Sciences, LLC.

North Brunswick, NJ 08902, USA.

Tel: +1-732-743-5936

Email: info@pblifesciences.com

Principal Display Panel

NDC: 69152-0515-1

Delivin 40

Number 515

Homeopathic Medicine

Relieves pain in lower abdomen

96 Pills (Approx.)

Product of USA